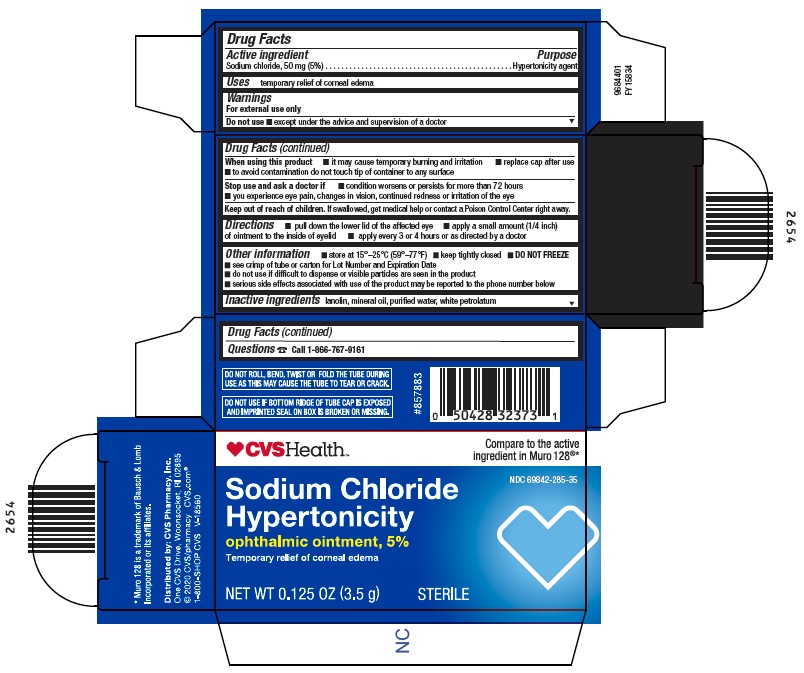 DRUG LABEL: Sodium Chloride Hypertonicity
NDC: 69842-285 | Form: OINTMENT
Manufacturer: CVS PHARMACY
Category: otc | Type: HUMAN OTC DRUG LABEL
Date: 20260115

ACTIVE INGREDIENTS: SODIUM CHLORIDE 50 mg/1 g
INACTIVE INGREDIENTS: LANOLIN; MINERAL OIL; WATER; PETROLATUM

Drug Facts

Active ingredient

Sodium chloride, 50 mg (5%)

Purpose

Hypertonicity agent

Uses

temporary relief of corneal edema

Warnings

For external use only

Do not use
▪except under the advice and supervision of a doctor

When using this product
▪it may cause temporary burning and irritation
▪replace cap after use
▪to avoid contamination do not touch tip of container to any surface

Stop use and ask a doctor if
▪condition worsens or persists for more than 72 hours
▪you experience eye pain, changes in vision, continued redness or irritation of the eye

Keep out of reach of children.

If swallowed, get medical help or contact a Poison Control Center right away.

Directions

▪pull down the lower lid of the affected eye
▪apply a small amount (1/4 inch) of ointment to the inside of eyelid
▪apply every 3 or 4 hours or as directed by a doctor

Other information

▪store at 15°-25°C (59°-77°F)
▪keep tightly closed
▪ DO NOT FREEZE
▪see crimp of tube or carton for Lot Number and Expiration Date
▪do not use if difficult to dispense or visible particles are seen in the product
▪serious side effects associated with use of the product may be reported to the phone number below

Inactive ingredients

lanolin, mineral oil, purified water, white petrolatum

Questions

[phone icon] Call 1-866-767-9161

Package/Label Principal Display Panel - Carton

[heart icon] CVSHealth™

Compare to the active
ingredient in Muro 128®*

NDC 69842-285-35

Sodium Chloride
Hypertonicity
ophthalmic ointment, 5%
Temporary relief of corneal edema

NET WT 0.125 OZ (3.5 g)

STERILE